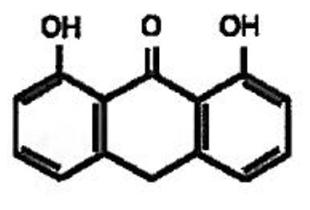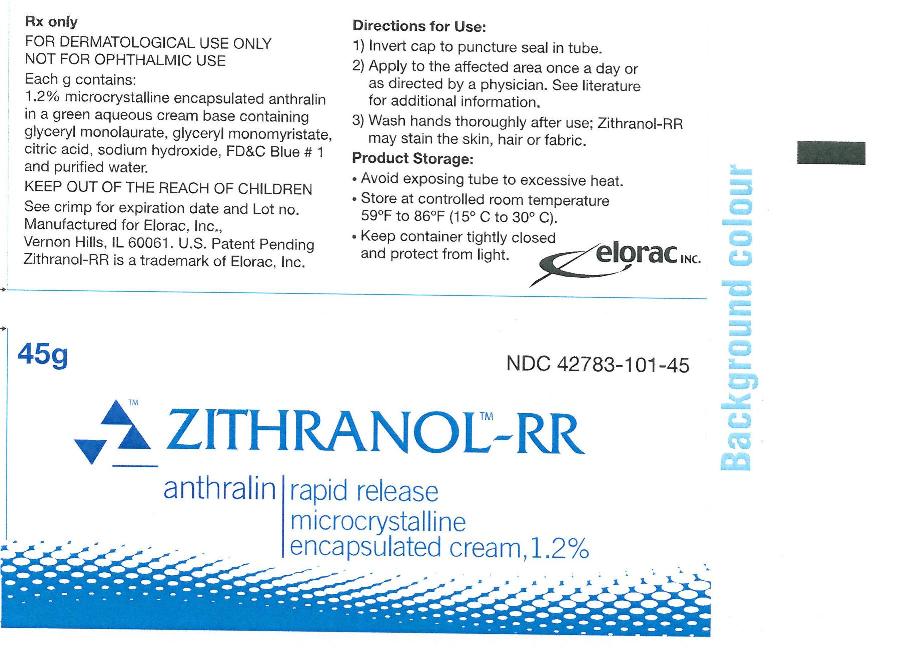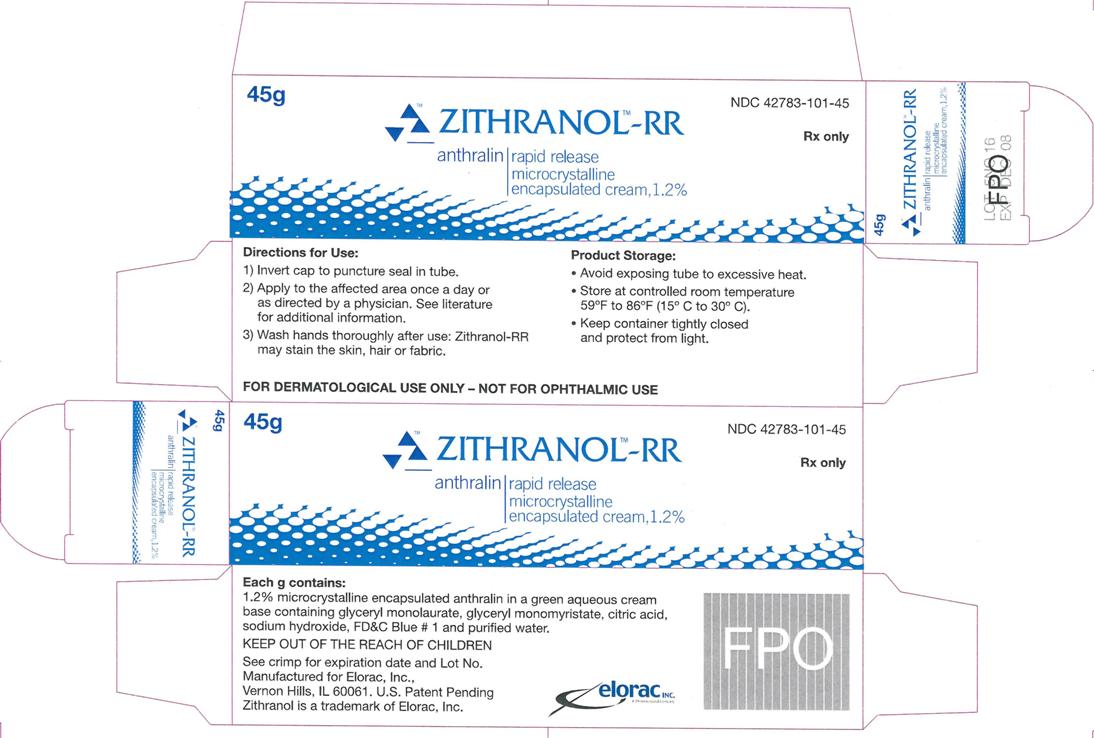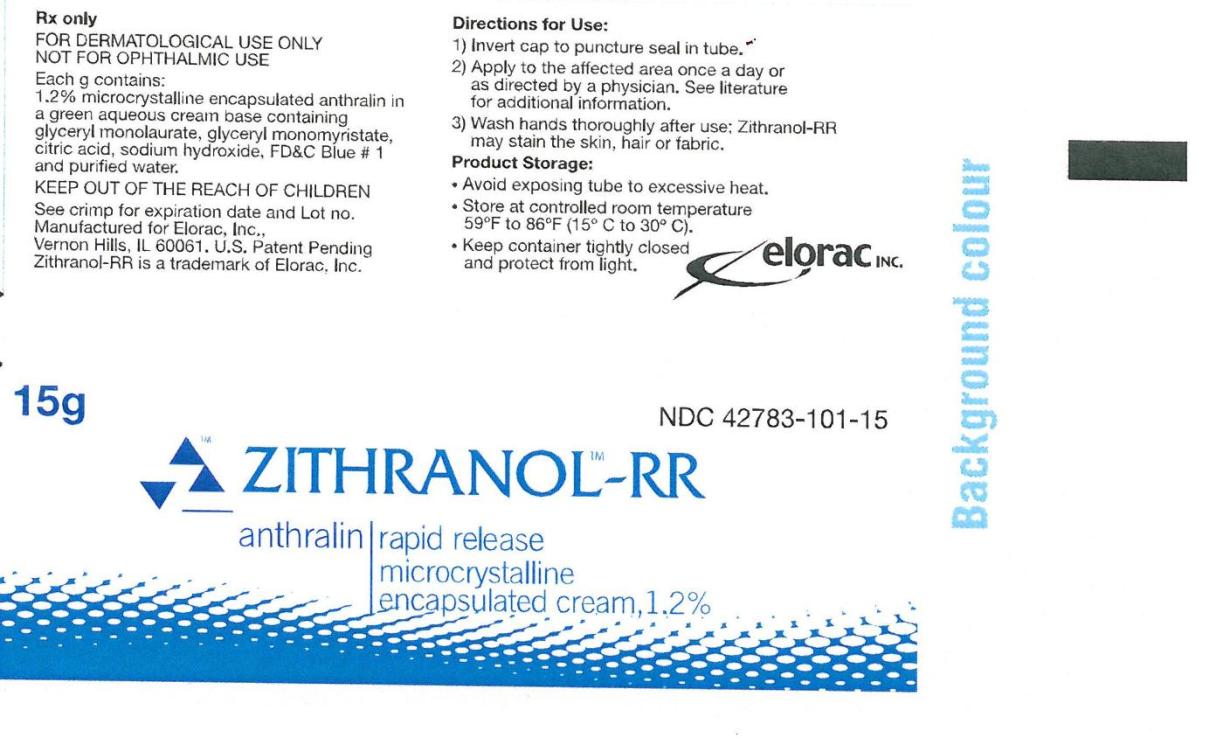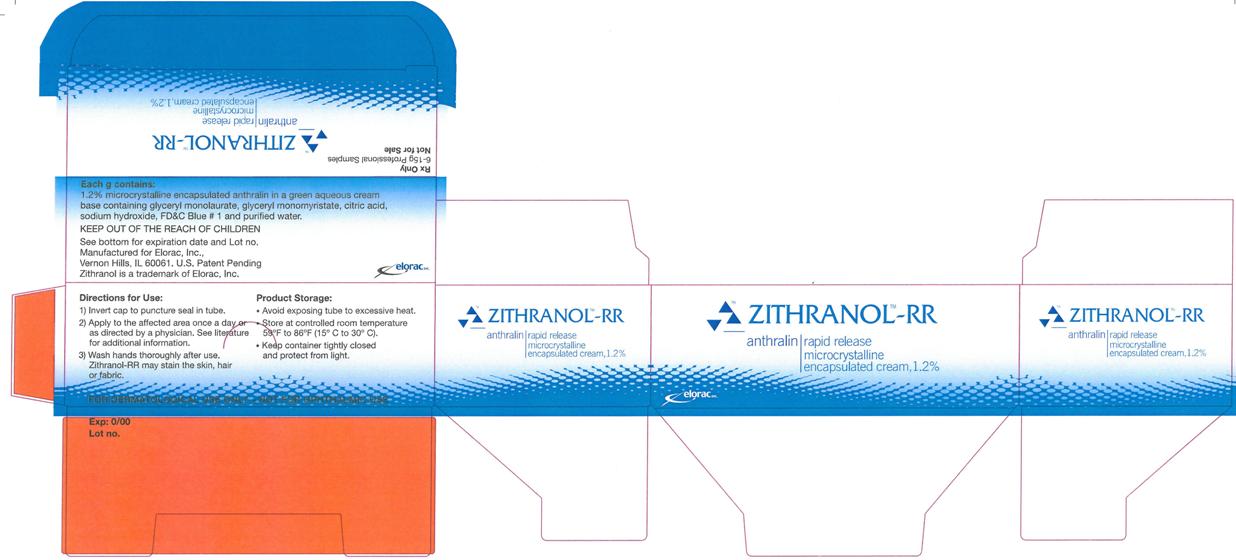 DRUG LABEL: ZITHRANOL-RR
NDC: 42783-101 | Form: cream
Manufacturer: Elorac Inc.
Category: prescription | Type: HUMAN PRESCRIPTION DRUG LABEL
Date: 20100129

ACTIVE INGREDIENTS: anthralin .012 g/1 g
INACTIVE INGREDIENTS: anhydrous citric acid

ZITHRANOL-RR anthralin microcrystalline encapsulated cream, 1.2% 45 g Container Label Principal Display Panel Text:

NDC 42783-101-45

ZITHRANOL-RR
anthralin microcrystalline encapsulated
cream, 1.2%
45 g

FOR DERMATOLOGIC USE ONLY
NOT FOR OPHTHALMIC USE

Rx only

ZITHRANOL-RR anthralin microcrystalline encapsulated cream, 1.2% 45 g Carton Label Principal Display Panel Text:

NDC 42783-101-45

ZITHRANOL-RR
anthralin microcrystalline encapsulated
cream, 1.2%
45 g

FOR DERMATOLOGIC USE ONLY
NOT FOR OPHTHALMIC USE

Rx only

ZITHRANOL-RR anthralin microcrystalline encapsulated cream, 1.2% 15 g Container Label Principal Display Panel Text:

NDC 42783-101-15

ZITHRANOL-RR
anthralin microcrystalline encapsulated
cream, 1.2%
15 g

FOR DERMATOLOGIC USE ONLY
NOT FOR OPHTHALMIC USE

Rx only

ZITHRANOL-RR anthralin microcrystalline encapsulated cream, 1.2% 15 g Carton Label Principal Display Panel Text:

NDC 42783-101-15

ZITHRANOL-RR
anthralin microcrystalline encapsulated
cream, 1.2%
15 g

FOR DERMATOLOGIC USE ONLY
NOT FOR OPHTHALMIC USE

Rx only

Package Insert ZITHRANOL-RR anthralin microcrystalline encapsulated cream, 1.2%

Rx only

FOR DERMATOLOGIC USE ONLY
NOT FOR OPHTHALMIC USE

DESCRIPTION

Zithranol-RR contains 1.2% microcrystalline encapsulated anthralin in a green aqueous cream base containing glyceryl monolaurate, glyceryl monomyristate, citric acid, sodium hydroxide, FD&C Blue No. 1 and purified water. The anthralin in Zithranol-RR is microencapsulated into a proprietary formulation of surface active crystalline polar lipids to provide for rapid release, as well as to reduce irritation and staining frequently observed with nonencapsulated anthralin preparations. Since the monoglycerides comprising the microcrystalline matrix have significant antimicrobial properties, Zithranol-RR is resistant to microbial contamination or overgrowth without the need for a preservative agent. The chemical name of anthralin is 1,8-dihydroxy-9-anthrone and its structural formula is:

CLINICAL PHARMACOLOGY

Zithranol-RR contains anthralin, a synthetic compound whose precise mechanism of anti-psoriatic action is not yet fully understood. However, numerous studies have demonstrated anti-proliferative and anti-inflammatory effects of anthralin on psoriatic and normal skin. The anti-proliferative effects of anthralin appear to result from both an inhibition of DNA synthesis as well as from its strong reducing properties. Recently, anthralin’s effectiveness as an anti-psoriatic agent has also been in part attributed to its abilities to induce lipid peroxidation and reduce levels of endothelial adhesion molecules which are markedly elevated in psoriatic patients. Unlike retinoids and PUVA, anthralin does not inhibit liver microsomal enzyme activity; consequently, the likelihood of adverse drug interactions is greatly reduced when other agents are administered concomitantly with anthralin.

Since Zithranol-RR’s proprietary microcrystalline delivery system rapidly releases anthralin into psoriatic plaques on contact with skin, Zithranol-RR is especially useful for short contact (5-15 minutes) therapy with anthralin.

INDICATIONS AND USAGE

For the topical treatment of patients with stable plaque psoriasis.

CONTRAINDICATIONS

Zithranol-RR is contraindicated for patients with acute or actively inflamed psoriatic eruptions or a history of hypersensitivity to any of the ingredients.

WARNINGS

Avoid contact with the eyes or mucous membranes. Exercise care when applying Zithranol-RR cream to the face or intertriginous skin areas. Discontinue use if a sensitivity reaction occurs or if excessive irritation develops.

PRECAUTIONS

General: To prevent the possibility of staining clothing or bed linen, it may be advisable to use protective dressings. To prevent discoloration of tub/shower, always rinse the tub/shower with lukewarm water immediately after washing/showering and then use a suitable cleanser to remove any deposit on the surface of the tub or shower. Contact with fabrics, plastics and other materials may cause staining and should be avoided. Always wash hands thoroughly after use. Keep container tightly capped when not in use. Avoid excessive heat. For external use only. Keep out of the reach of children.

Carcinogenesis, mutagenesis, impairment of fertility: Long-term studies in animals have not been performed to evaluate the carcinogenic potential of the drug. Although anthralin has been found to have tumor-promoting properties on mouse skin, there have been no reports to suggest carcinogenic effects in humans after many years of clinical use.

Pregnancy
Teratogenic Effects: Pregnancy Category C
Animal reproduction studies have not been conducted with Zithranol-RR cream. It is also not known whether Zithranol-RR cream can cause fetal harm when administered to a pregnant woman or can affect reproduction capacity. Zithranol-RR cream should be given to a pregnant woman only if clearly needed.

Nursing mothers: It is not known whether this drug is excreted in human milk. Because many drugs are excreted in milk and because of the potential for tumorigenicity shown for anthralin in animal studies, a decision should be made whether to discontinue nursing or to discontinue the drug, taking into account the importance of the drug to the mother.

Pediatric use: Safety and effectiveness in children have not been established.

ADVERSE REACTIONS

Very few instances of contact allergic reactions to anthralin have been reported. Transient primary irritation and staining of normal or uninvolved skin surrounding the treated lesions, which is frequently seen with other anthralin preparations is less common with Zithranol-RR due to microcrystalline coating of the anthralin particles. If the initial treatment produces excessive soreness or if the lesions spread, reduce frequency of application and, in extreme cases, discontinue use and consult a physician. Some temporary discoloration of hair and fingernails may arise during the period of treatment but should be minimized by careful application. Staining of fabrics may be permanent, so contact should be avoided.

DOSAGE AND ADMINISTRATION

Generally, it is recommended that Zithranol-RR cream be applied once a day. Anthralin is known to be a potential skin irritant. The irritant potential of anthralin is directly related to the strength being used, the time of contact, and each patient’s individual tolerance. Where the response to anthralin treatment has not previously been established, commence treatment using a short contact time (5 – 15 min.) for at least one week. When a short contact time is used initially, it can be increased stepwise to thirty minutes before removing the cream by washing or showering. The optimal period of contact will vary according to the patient’s response to treatment.

For the skin: Apply sparingly to the psoriatic lesions avoiding normal skin and rub gently and carefully into the skin. Avoid applying an excessive quantity which may cause unnecessary soiling and staining of the clothing and/or bed linen. At the end of each period of treatment, rinse the skin thoroughly with cool to lukewarm water before washing with soap. The margins of the lesions may gradually become stained purple/brown as treatment progresses, but this will disappear after cessation of treatment.

For the scalp: Wash the hair with shampoo, rinse with water and apply Zithranol-RR cream while the hair is still damp. Rub the cream well into the psoriatic lesions. Keep Zithranol-RR cream away from the eyes. Care should be taken to avoid application to uninvolved scalp margins. Remove any unintended residue which may be deposited behind the ears. At the end of each period of contact, rinse hair and scalp thoroughly with cool to lukewarm water and then shampoo the hair and scalp to remove any surplus cream. This treatment may be repeated on alternate days if necessary.

HOW SUPPLIED

Zithranol-RR (anthralin) microcrystalline encapsulated cream, 1.2% is supplied in tubes.

45g NDC 42783-101-45
15g NDC 42783-101-15

Store at controlled room temperature 59°F to 86°F (15°C to 30°C).

Manufactured for:
Elorac, Inc.
Vernon Hills, IL 60061

U.S. Patent Pending

Caution: Federal law prohibits dispensing without prescription.

07/2008